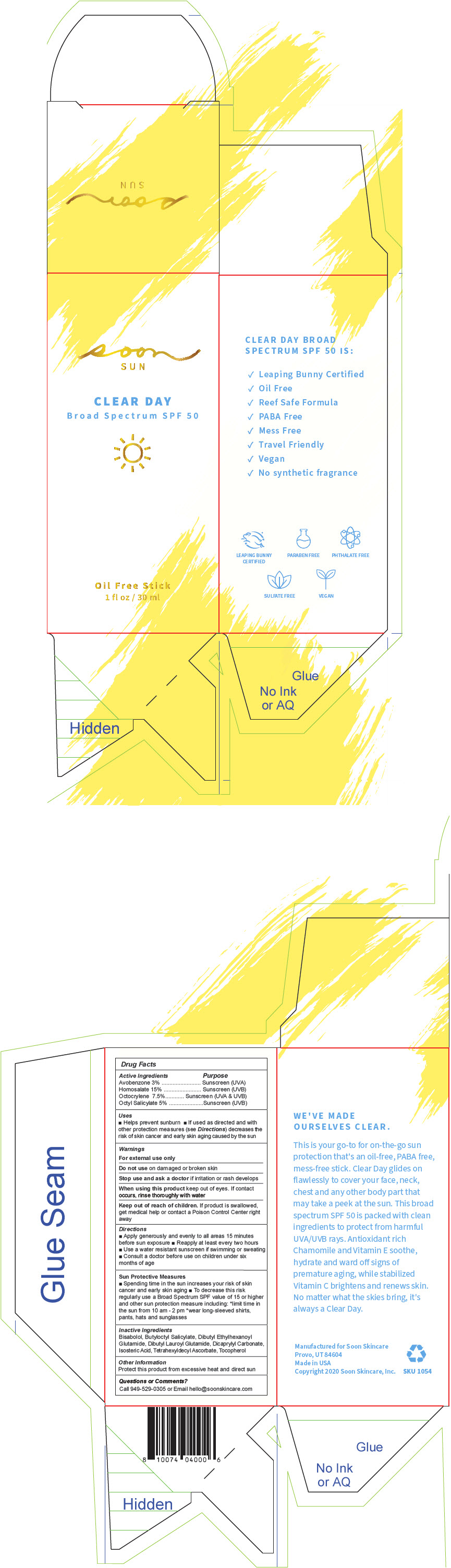 DRUG LABEL: Clear Day 
NDC: 82079-001 | Form: GEL
Manufacturer: Soon Skin Care, Inc.
Category: otc | Type: HUMAN OTC DRUG LABEL
Date: 20210824

ACTIVE INGREDIENTS: Avobenzone 0.9 mg/30 mL; OCTISALATE 1.5 mg/30 mL; Octocrylene 2.25 mg/30 mL; HOMOSALATE 4.5 mg/30 mL
INACTIVE INGREDIENTS: Dicaprylyl Carbonate; Isostearic Acid; Dibutyl Lauroyl Glutamide; Butyloctyl Salicylate; Dibutyl Ethylhexanoyl Glutamide; .ALPHA.-BISABOLOL, (+/-)-; .ALPHA.-TOCOPHEROL, DL-; TETRAHEXYLDECYL ASCORBATE

Clear Day
Soon Sun

Drug Facts

ACTIVE INGREDIENT

Active Ingredients | Purpose
Avobenzone 3% | Sunscreen (UVA)
Homosalate 15% | Sunscreen (UVB)
Octocrylene 7.5% | Sunscreen (UVA & UVB)
Octyl Salicylate 5% | Sunscreen (UVB)

Uses

- Helps prevent sunburn
- If used as directed and with other protection measures (see Directions) decreases the risk of skin cancer and early skin aging caused by the sun

Warnings

For external use only

Do not use on damaged or broken skin

Stop use and ask a doctor if irritation or rash develops

When using this product keep out of eyes. If contact occurs, rinse thoroughly with water

Keep out of reach of children. If product is swallowed, get medical help or contact a Poison Control Center right away

Directions

- Apply generously and evenly to all areas 15 minutes before sun exposure
- Reapply at least every two hours
- Use a water resistant sunscreen if swimming or sweating
- Consult a doctor before use on children under six months of age

Sun Protective Measures

- Spending time in the sun increases your risk of skin cancer and early skin aging
- To decrease this risk regularly use a Broad Spectrum SPF value of 15 or higher and other sun protection measure including: *limit time in the sun from 10 am - 2 pm *wear long-sleeved shirts, pants, hats and sunglasses

Inactive Ingredients

Bisabolol, Butyloctyl Salicylate, Dibutyl Ethylhexanoyl Glutamide, Dibutyl Lauroyl Glutamide, Dicaprylyl Carbonate, Isosteric Acid, Tetrahexyldecyl Ascorbate, Tocopherol

Other Information

Protect this product from excessive heat and direct sun

Questions or Comments?

Call 949-529-0305 or Email hello@soonskincare.com

PRINCIPAL DISPLAY PANEL - 30 ml Bottle Box

soon
SUN

CLEAR DAY
Broad Spectrum SPF 50

Oil Free Stick
1 fl oz / 30 ml